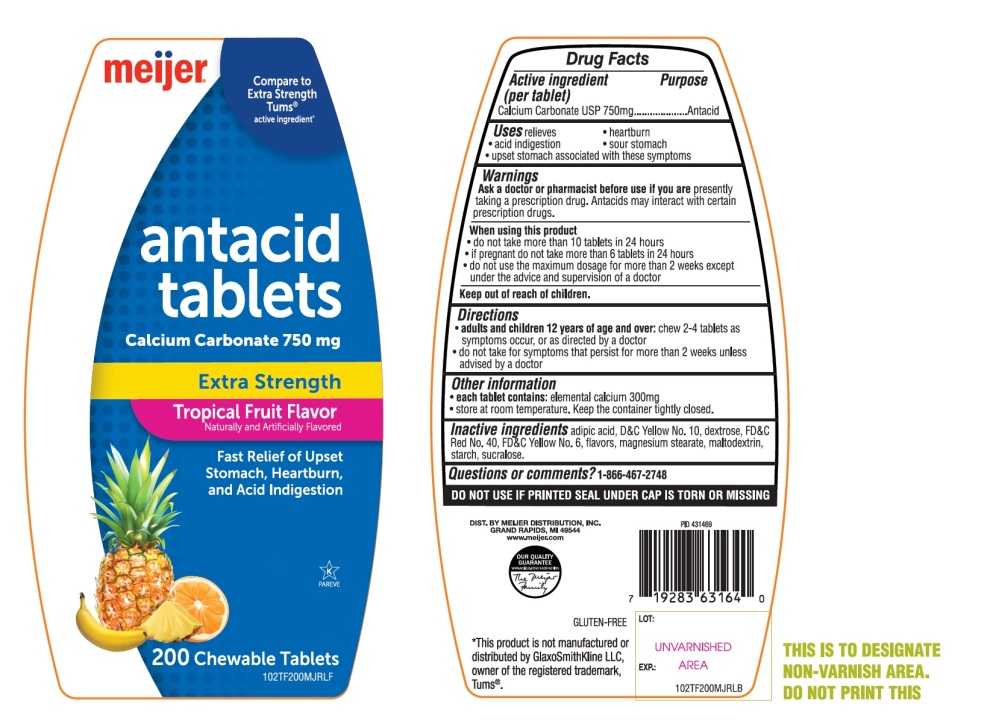 DRUG LABEL: Meijer Extra Strength

NDC: 41250-203 | Form: TABLET, CHEWABLE
Manufacturer: MEIJER DISTRIBUTION INC
Category: otc | Type: HUMAN OTC DRUG LABEL
Date: 20251024

ACTIVE INGREDIENTS: CALCIUM CARBONATE 750 mg/1 1
INACTIVE INGREDIENTS: ADIPIC ACID; D&C YELLOW NO. 10; DEXTROSE, UNSPECIFIED FORM; FD&C RED NO. 40; FD&C YELLOW NO. 6; MAGNESIUM STEARATE; MALTODEXTRIN; STARCH, CORN; SUCRALOSE

Meijer Extra Strength Tropical Fruit Antacid 200 Tabs Drug Facts

Active ingredient (per tablet)

Calcium Carbonate USP 750mg

Purpose

Antacid

Uses

relieves

- heartburn
- acid indigestion
- sour stomach
- upset stomach associated with these symptoms

Warnings

Ask a doctor or pharmacist before use if you are

presently taking a prescription drug. Antacids may interact with certain prescription drug.

When using this product

- do not take more than 10 tablets in 24 hours
- if pregnant do not take more than 6 tablets in 24 hours
- do not use the maximum dosage for more than 2 weeks except under the advice and supervision of a doctor

Directions

- adults and children 12 years of age and over:chew 2-4 tablets as symptoms occur, or as directed by a doctor.
- do not take for symptoms that persist for more than 2 weeks unless advised by a doctor

Other information

- each tablet contains:elemental calcium 300mg
- Store at room temperature. Keep the container tightly closed.

Inactive ingredients

adipic acid, D&C Yellow No. 10, dextrose, FD&C Red No. 40, FD &C Yellow No. 6, flavors, magnesium stearate, maltodextrin, starch, sucralose.

Questions or comments?

1-866-467-2748

Safety Sealed: DO NOT USE IF PRINTED SEAL UNDER CAP IS TORN OR MISSING.

Principal Display Panel

Compare to Extra Strength Tums® active ingredient*

meijer®

NDC# 41250-203-20

antacid tablets

Calcium Carbonate 750 mg

Extra Strength

Tropical Fruit Flavors

Naturally and Artificially Flavored

Fast Relief of Upset Stomach, Heartburn and Acid Indigestion

200 CHEWABLE TABLETS

GLUTEN-FREE

OUR QUALITY GUARANTEED

WWW.MEIJER.COM/SATISFACTION

K PAREVE

DIST. BY MEIJER DISTRIBUTION, INC

GRAND RAPIDS, MI 49544

www.meijer.com

*This product is not manufactured or distributed by GlaxoSmithKline LLC, owner of the registered trademark, Tums®.